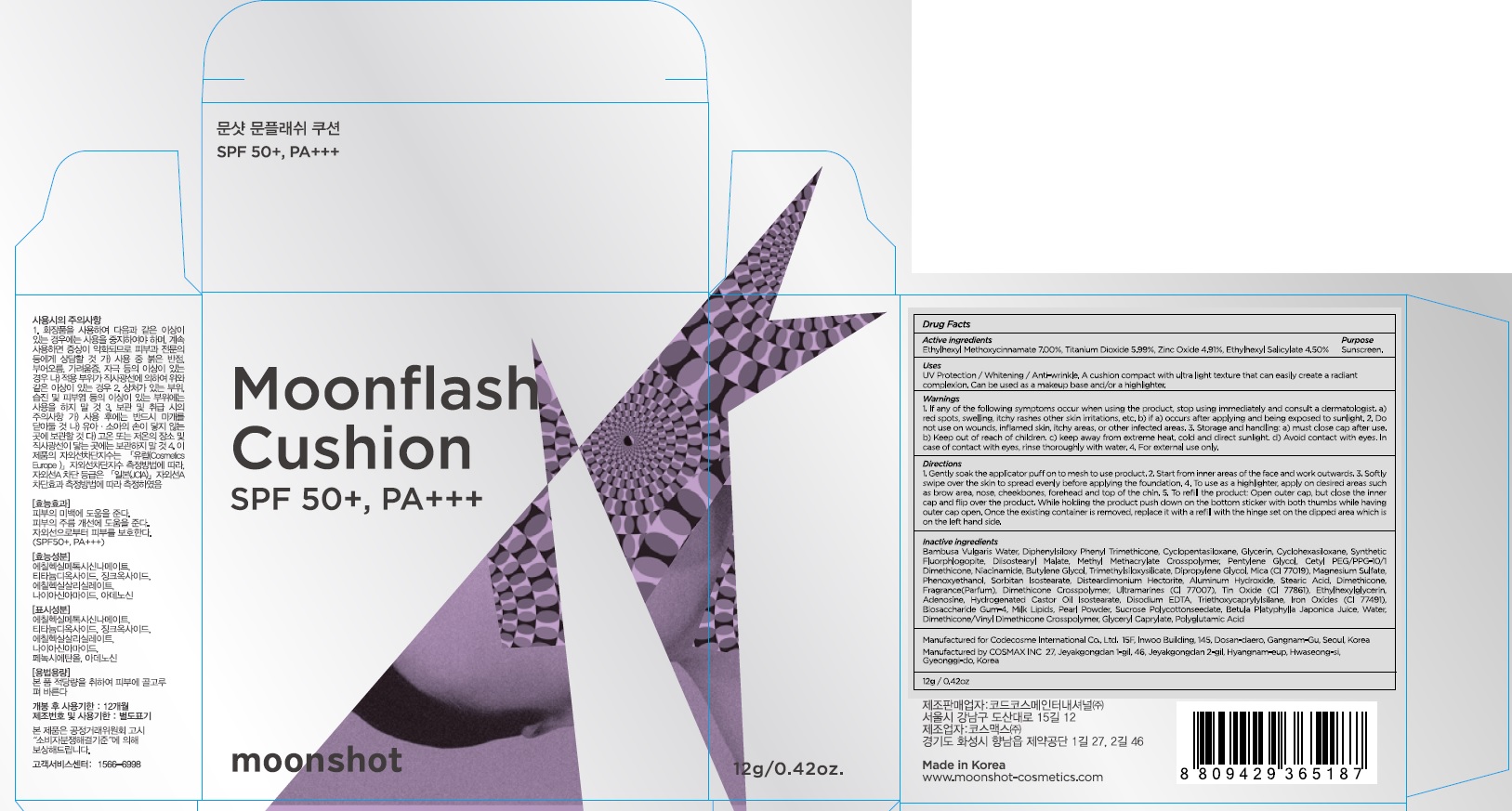 DRUG LABEL: Moonflash Cushion
NDC: 71786-050 | Form: POWDER
Manufacturer: Codecosme International Co., Ltd.
Category: otc | Type: HUMAN OTC DRUG LABEL
Date: 20171018

ACTIVE INGREDIENTS: Octinoxate 0.84 g/12 g; Titanium Dioxide 0.71 g/12 g; Zinc Oxide 0.58 g/12 g; Octisalate 0.54 g/12 g
INACTIVE INGREDIENTS: Glycerin; Diisostearyl Malate

ACTIVE INGREDIENT

Active ingredients: Ethylhexyl Methoxycinnamate 7.00%, Titanium Dioxide 5.99%, Zinc Oxide 4.91%, Ethylhexyl Salicylate 4.50%

INACTIVE INGREDIENT

Inactive ingredients: Bambusa Vulgaris Water, Diphenylsiloxy Phenyl Trimethicone, Cyclopentasiloxane, Glycerin, Cyclohexasiloxane, Synthetic Fluorphlogopite, Diisostearyl Malate, Methyl Methacrylate Crosspolymer, Pentylene Glycol, Cetyl PEG/PPG-10/1 Dimethicone, Niacinamide, Butylene Glycol, Trimethylsiloxysilicate, Dipropylene Glycol, Mica (CI 77019), Magnesium Sulfate, Phenoxyethanol, Sorbitan Isostearate, Disteardimonium Hectorite, Aluminum Hydroxide, Stearic Acid, Dimethicone, Fragrance(Parfum), Dimethicone Crosspolymer, Ultramarines (CI 77007), Tin Oxide (CI 77861), Ethylhexylglycerin, Adenosine, Hydrogenated Castor Oil Isostearate, Disodium EDTA, Triethoxycaprylylsilane, Iron Oxides (CI 77491), Biosaccharide Gum-4, Milk Lipids, Pearl Powder, Sucrose Polycottonseedate, Betula Platyphylla Japonica Juice, Water, Dimethicone/Vinyl Dimethicone Crosspolymer, Glyceryl Caprylate, Polyglutamic Acid

PURPOSE

Purpose: Sunscreen

WARNINGS

Warnings: 1. If any of the following symptoms occur when using the product, stop using immediately and consult a dermatologist. a) red spots, swelling, itchy rashes other skin irritations, etc. b) if a) occurs after applying and being exposed to sunlight. 2. Do not use on wounds, inflamed skin, itchy areas, or other infected areas. 3. Storage and handling: a) must close cap after use. b) Keep out of reach of children. c) keep away from extreme heat, cold and direct sunlight. d) Avoid contact with eyes. In case of contact with eyes, rinse thoroughly with water. 4. For external use only.

DESCRIPTION

Uses: UV Protection / Whitening / Anti-wrinkle. A cushion compact with ultra light texture that can easily create a radiant complexion. Can be used as a makeup base and/or a highlighter.

Directions: 1. Gently soak the applicator puff on to mesh to use product. 2. Start from inner areas of the face and work outwards. 3. Softly swipe over the skin to spread evenly before applying the foundation. 4. To use as a highlighter, apply on desired areas such as brow area, nose, cheekbones, forehead and top of the chin. 5. To refill the product: Open outer cap, but close the inner cap and flip over the product. While holding the product push down on the bottom sticker with both thumbs while having outer cap open. Once the existing container is removed, replace it with a refill with the hinge set on the dipped area which is on the left hand side.